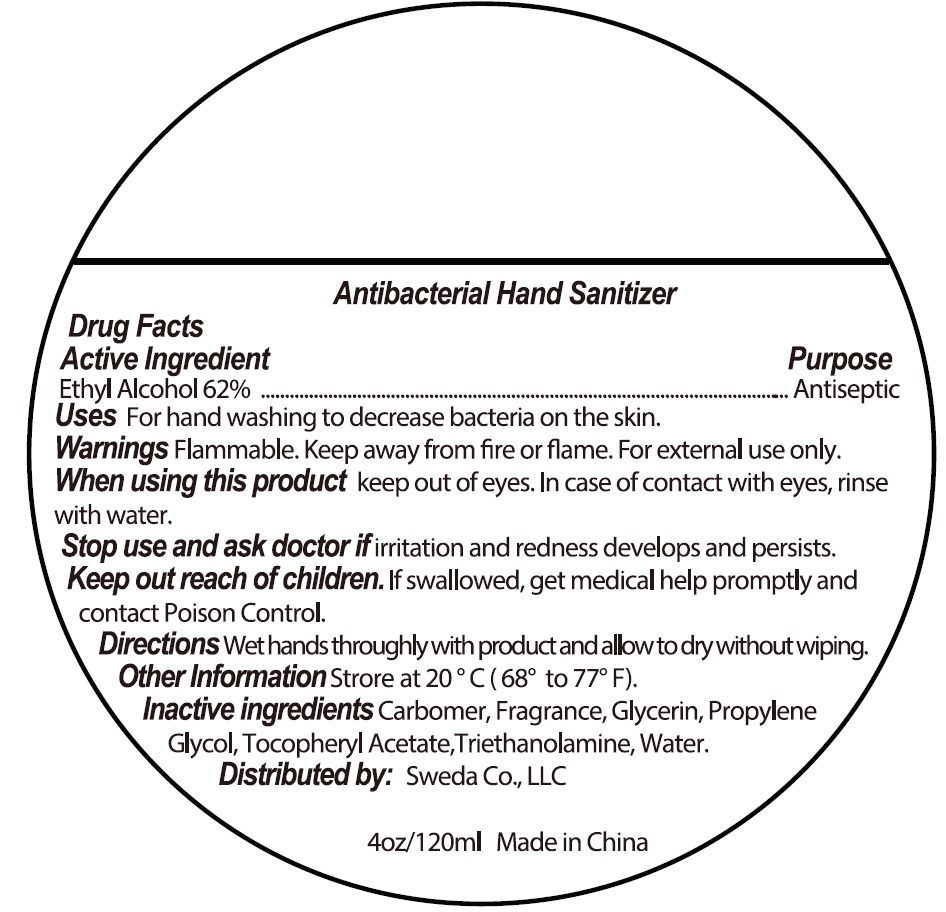 DRUG LABEL: Antibacterial Hand Sanitizer
NDC: 90121-003 | Form: GEL
Manufacturer: Sweda Company LLC
Category: otc | Type: HUMAN OTC DRUG LABEL
Date: 20200831

ACTIVE INGREDIENTS: ALCOHOL 0.62 mL/1 mL
INACTIVE INGREDIENTS: CARBOMER HOMOPOLYMER, UNSPECIFIED TYPE; GLYCERIN; PROPYLENE GLYCOL; .ALPHA.-TOCOPHEROL ACETATE; TROLAMINE; WATER

Antibacterial Hand Sanitizer

Active Ingredient

Ethyl Alcohol 62%

Purpose

Antiseptic

Uses

For hand washing to decrease bacteria on the skin.

Warnings:

Flammable. Keep away from fire or flame. For External use only

When using this product,

keep out of eyes. In case of contact with eyes, rinse with water.

Stop use and ask a doctor

if irritation and redness develops and persists.

Keep out of reach of children.

If swallowed, get medical help promptly and contact poison Control.

Directions

Wet hands thoroughly with product allow to dry without wiping.

Other Information

Store at 20°C (68°-77°F).

Inactive Ingredients:

Carbomer, Fragrance, Glycerin, Propylene Glycol, Tocopheryl acetate, Triethanolamine, Water.